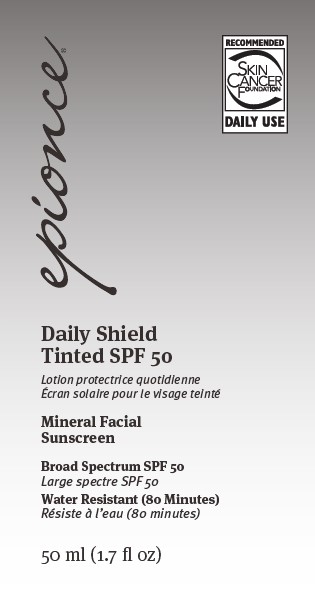 DRUG LABEL: Epionce Daily Shield
NDC: 42673-005 | Form: LOTION
Manufacturer: Episciences, Inc.
Category: otc | Type: HUMAN OTC DRUG LABEL
Date: 20251202

ACTIVE INGREDIENTS: ZINC OXIDE 0.093 g/1 g; TITANIUM DIOXIDE 0.048 g/1 g
INACTIVE INGREDIENTS: BUTYLENE GLYCOL; CAPRYLYL TRISILOXANE; CETYL PEG/PPG-10/1 DIMETHICONE (HLB 2); CYCLOMETHICONE 5; DISTEARDIMONIUM HECTORITE; ETHYLHEXYLGLYCERIN; FERRIC OXIDE RED; FERRIC OXIDE YELLOW; LEVOMENOL; PEG/PPG-18/18 DIMETHICONE; PEG-10 DIMETHICONE (600 CST); PHENOXYETHANOL; POLYMETHYLSILSESQUIOXANE (4.5 MICRONS); PROPYLENE CARBONATE; FERROSOFERRIC OXIDE; GLYCERIN; HELIANTHUS ANNUUS FLOWERING TOP; HEXYLENE GLYCOL; ISODODECANE; METHICONE (20 CST); SILICON DIOXIDE; TOCOPHEROL; TRIETHOXYCAPRYLYLSILANE; WATER; SODIUM HYDROXIDE; RICE BRAN; CAPRYLYL GLYCOL; ROSEMARY; ALPHA-TOCOPHEROL ACETATE; SODIUM CHLORIDE; DIMETHICONE CROSSPOLYMER (450000 MPA.S AT 12% IN CYCLOPENTASILOXANE); ALUMINUM OXIDE; APPLE; ARGAN OIL

Epionce Daily Shield Tinted SPF 50

Active ingredients

Titanium Dioxide 4.8%
Zinc Oxide 9.3%

Purpose

Sunscreen

Uses

- helps prevent sunburn
- if used as directed with other sun protection
  measures (see Directions), decreases the risk of
  skin cancer and early skin aging caused by the sun.

Warnings

For external use only

Do not use

- on damaged or broken skin

Stop use and ask a doctor if

- rash occurs

When using this product

- keep out of eyes.
  Rinse with water to remove.

Keep out of reach of children.

If product is swallowed, get medical help or contact a Poison Control Center right away.

Directions

- apply liberally 15 minutes before sun exposure
- reapply:
  - after 80 minutes of swimming or sweating
  - immediately after towel drying
  - at least every two hours
- children under 6 months: Ask a doctor
- Sun Protection Measures. Spending time in the
  sun increases your risk of skin cancer and early
  skin aging. To decrease this risk, regularly use a
  sunscreen with a Broad Spectrum SPF value of
  15 or higher and other sun protection measures
  including:
  - limit time in the sun, especially from 10 a.m. - 2 p.m.
  - wear long-sleeved shirts, pants, hats and
    sunglasses

Other information

- protect the product in this container from
  excessive heat and direct sun

Inactive ingredients

Cyclopentasiloxane, Water, Dimethicone

Crosspolymer, Butylene Glycol, Cetyl

PEG/PPG-10/1 Dimethicone,

Polymethylsilsesquioxane, Caprylyl

Methicone, PEG-10 Dimethicone, Argania

Spinosa Kernel Oil, Glycerin, Disteardimonium

Hectorite, Isododecane, Tocopheryl Acetate,

Sodium Chloride, Alumina, Bisabolol, Caprylyl

Glycol, Ethylhexylglycerin, Helianthus Annuus

(Sunflower) Extract, Hexylene Glycol,

Hydrogen Dimethicone, Lauryl Polyglyceryl-3

Polydimethylsiloxyethyl Dimethicone, Oryza

Sativa (Rice) Bran Extract, PEG/PPG-18/18

Dimethicone, Phenoxyethanol, Propylene

Carbonate, Pyrus Malus (Apple) Fruit Extract,

Rosmarinus Officinalis (Rosemary) Leaf

Extract, Silica,Tocopherol,

Triethoxycaprylylsilane, Iron Oxides

(C.I. 77491), Iron Oxides (C.I. 77492), Iron

Oxides (C.I. 77499)

.

Questions?

Call toll free 1-866-374-6623